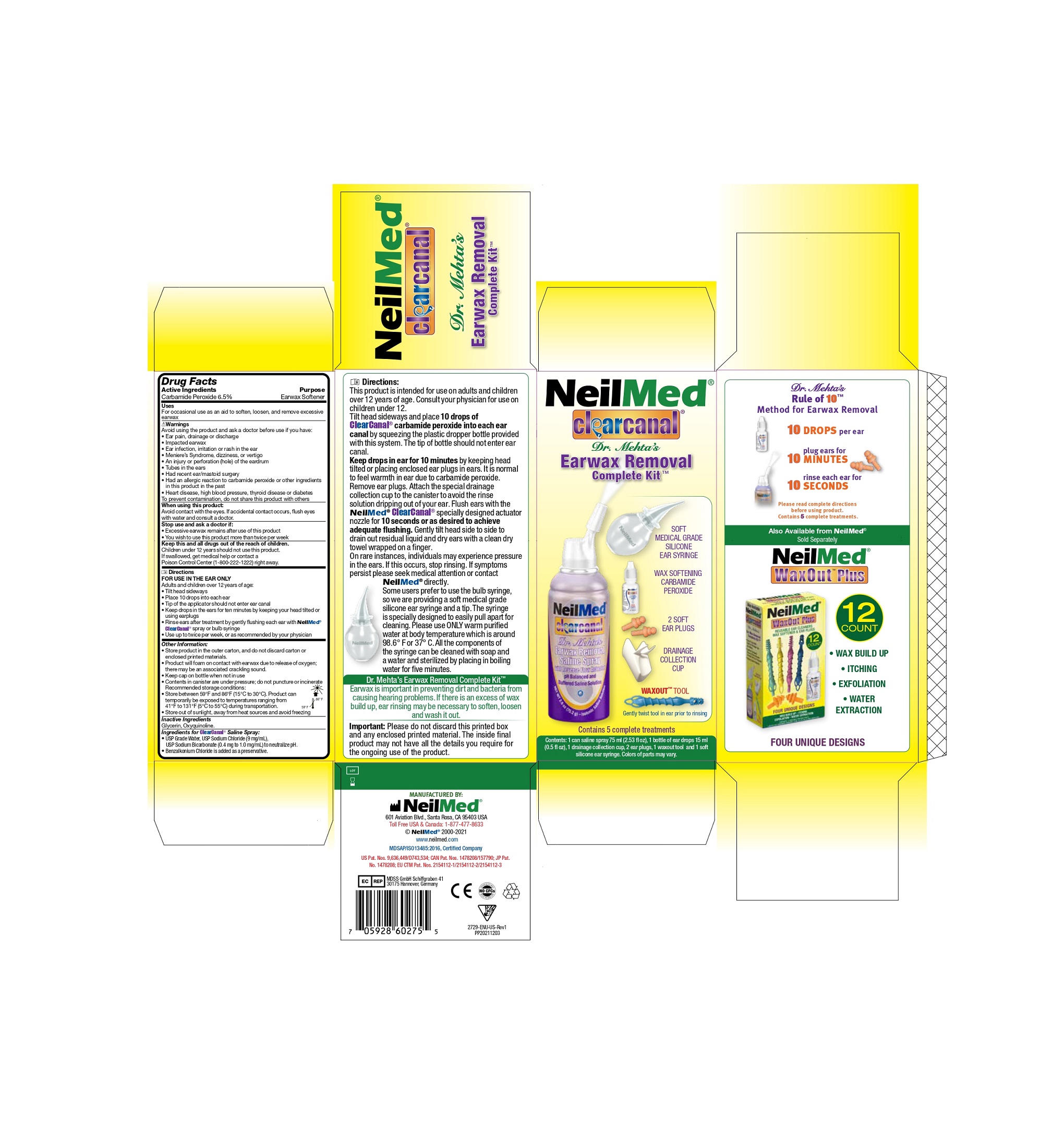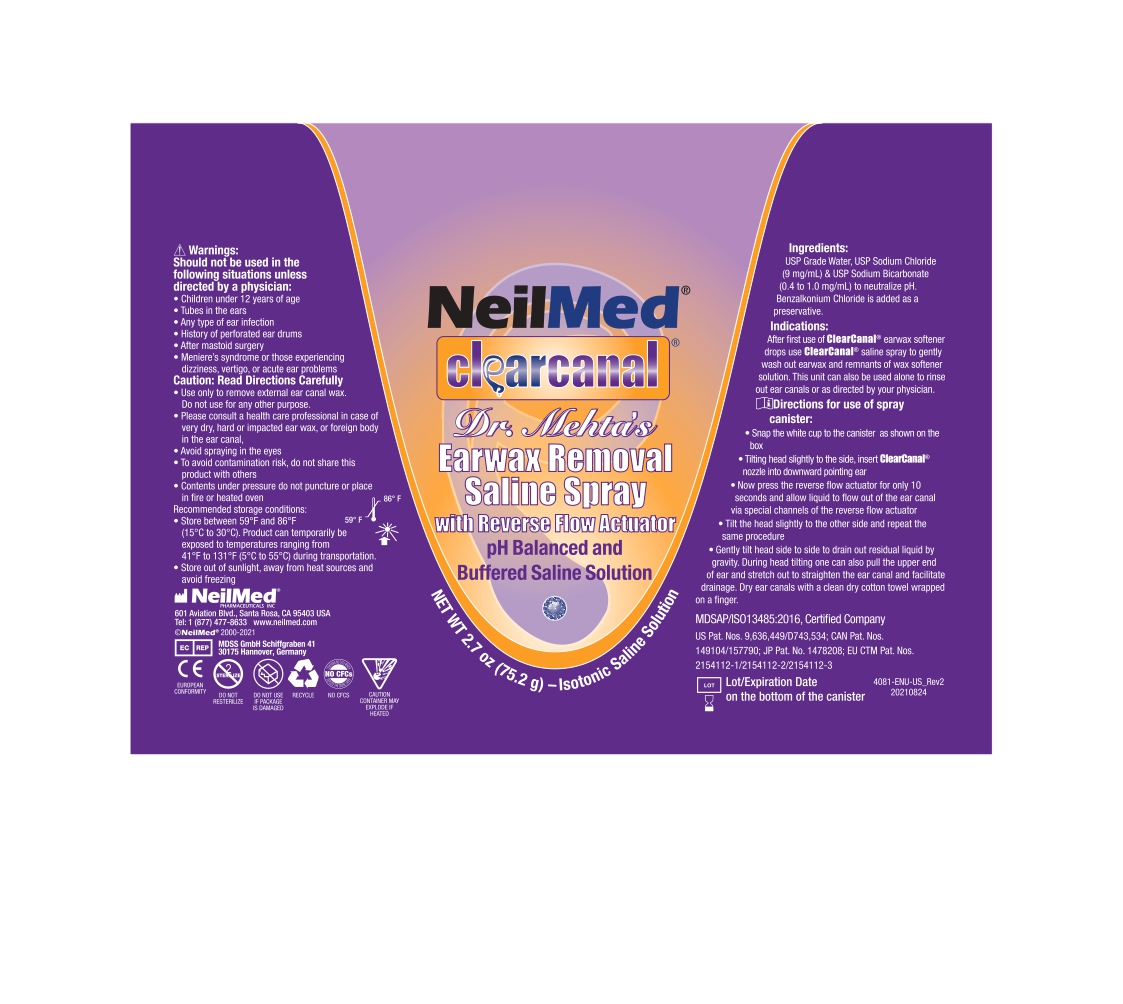 DRUG LABEL: NeilMed Clear Canal Earwax Removal kit
NDC: 13709-314 | Form: SOLUTION/ DROPS
Manufacturer: NEILMED PHARMACEUTICALS INC
Category: otc | Type: HUMAN OTC DRUG LABEL
Date: 20240111

ACTIVE INGREDIENTS: CARBAMIDE PEROXIDE 65 mg/1 mL
INACTIVE INGREDIENTS: GLYCERIN; OXYQUINOLINE

NeilMed ClearCanal EarWax Removal Complete Kit (BKC)

Drug Facts

Active Ingredients

Carbamide Peroxide 6.5%

Purpose

Earwax Softener

Uses

For occasional use as an aid to soften, loosen, and remove excessive earwax.

! Warnings

Avoid using the product and ask a doctor before use if you have :

- Ear pain, drainage or discharge
- Impacted earwax
- Ear infection, irritation or rash in the ear.
- Meniere's Syndrome, dizziness, or vertigo
- An injury or perforation (hole) of the eardrum
- Tubes in the ears
- Has recent ear/mastoid surgery
- Had an allergic reaction to carbamide peroxide or other ingredients in this product in the past.
- Heart disease, high blood pressure, thyroid disease or diabetes

To prevent contamination, do not share this product with others.

When using this product:

Avoid contact with the eyes. If accidental contact occurs, flush eyes with water and consult a doctor.

Stop use and ask a doctor if:

- Excessive earwax remains after use of this product
- You wish to use this product more than twice per week

Keep this and all drugs out of the reach of children

Children under 12 years should not use this product.

If swallowed, get medical help or contact a Poison Control Center (1-800-222-1222) right away.

Directions FOR USE IN THE EAR ONLY

Adults and children over 12 years of age:

- Tilt head sideways
- Place 10 drops into each ear
- Tip of the applicator should not enter ear canal
- Keep drops in the ears for ten minutes by keeping your head tilted or using earplugs
- Rinse ears after treatment by gently flusing each ear with NeilMed®ClearCanal® spray or bulb syringe
- Use up to twice per week, or as recommended by your physician.

Other Information:

- Store product in the outer carton, and do not discard carton or enclosed printed materials.
- Product will foam on contact with earwax due to release of oxygen; there may be an associated crackling sound.
- Keep cap on bottle when not in use.
- Contents in canister are under pressure; do not puncture or incinerate

Recommended storage conditions:

- Store between 59°F and 86°F (15°C to 30°C). Product can temporarily be exposed to temperatures ranging from 41ºF to 131ºF (5ºC to 55ºC) during transportation.
- Store out of sunlight, away from heat sources and avoid freezing

Inactive Ingredients

Glycerin, Oxyquinoline

Ingredients for ClearCanal® Saline Spray :

- USP Grade Water, USP Sodium Chloride (9mg/ml), USP Sodium Bicarbonate (0.4mg to 1.0mg/ml) to neutralize pH.
- Benzalkonium Chloride is added as a preservative

Contents :

1 can saline spray 75ml (2.53 fl oz), 1 bottle of ear drops 15ml (0.5 fl oz), 1 drainage collection cup, 2 ear plugs, 1 waxout tool and 1 soft silicone ear syringe. Colors of parts may vary.

Directions:

This product is intended for use on adults and children over 12 years of age. Consult your physician for use on children under 12.

Tilt head sideways and place 10 drops of ClearCanal Carbamide peroxide into each ear canal by squeezing the plastic dropper bottle provided with this system. The tip of bottle should not enter ear canal.

Keep drops in ear for 10 minutes by head tilted or placing enclosed ear plugs in ears. It is normal to feel warmth in ear due to carbamide peroxide. Remove ear plugs. Attach the special drainage collection cup to the canister to avoid the rinse solution dripping out of your ear. Flush ears with the NeilMed ClearCanal specially designed actuator nozzle for 10 seconds or as desired to achieve adequate flushing. Gently tilt head side to side to drain out residual liquid and dry ears with a clean dry towel wrapped on a finger.